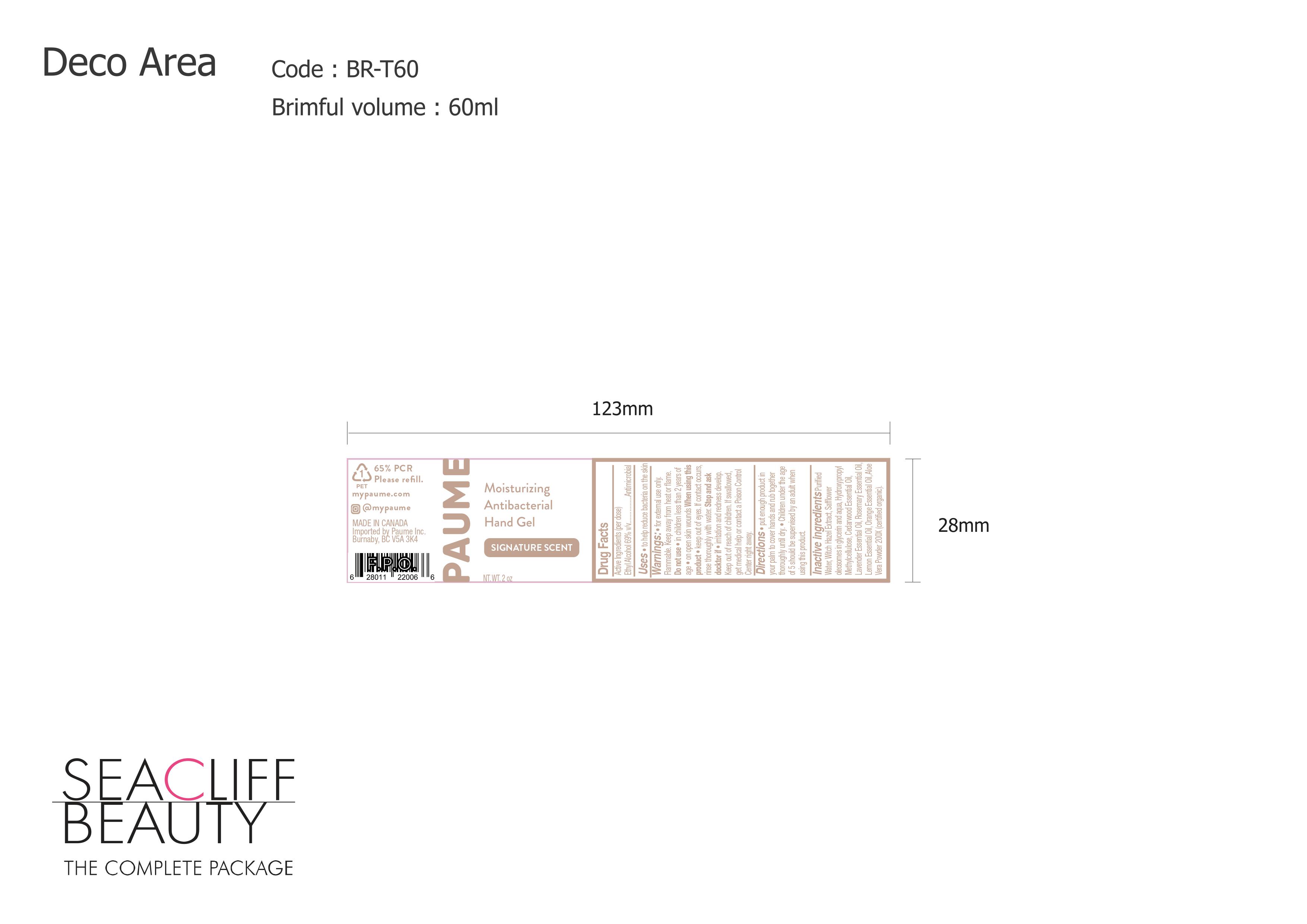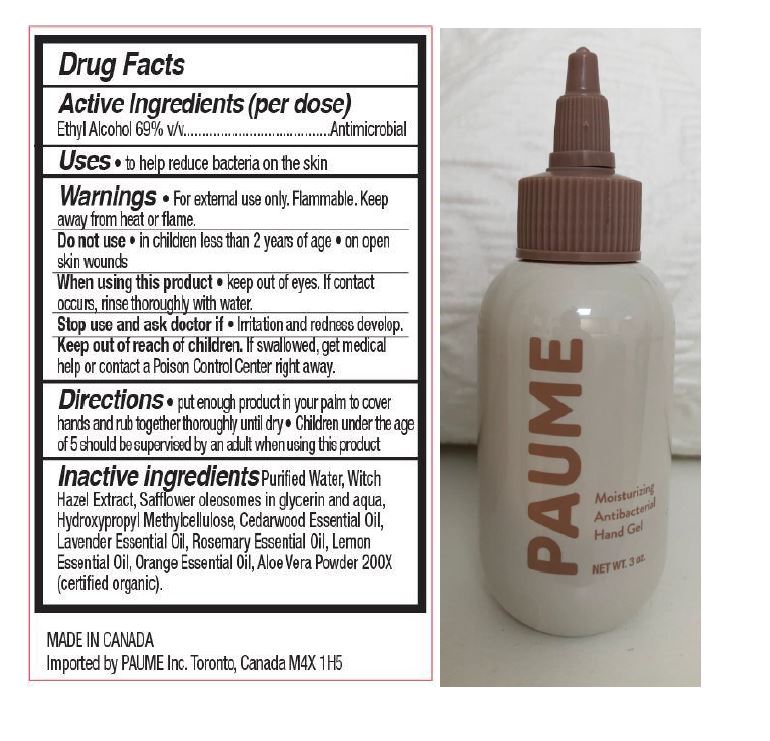 DRUG LABEL: Paume Moisturizing Antibacterial Hand Gel
NDC: 80328-123 | Form: GEL
Manufacturer: Paume Inc
Category: otc | Type: HUMAN OTC DRUG LABEL
Date: 20250522

ACTIVE INGREDIENTS: ALCOHOL 69 mL/100 mL
INACTIVE INGREDIENTS: ORANGE OIL; ALOE VERA LEAF; WATER; LAVENDER OIL; CEDRUS ATLANTICA BARK OIL; ROSEMARY OIL; CARTHAMUS TINCTORIUS (SAFFLOWER) OLEOSOMES; WITCH HAZEL; LEMON OIL; HYPROMELLOSE, UNSPECIFIED

ACTIVE INGREDIENT

Ethyl alcohol 69% v/v

Keep out of reach of children. If swallowed, get medical help or contact a Poison Control Center right away.

DOSAGE AND ADMINISTRATION

Put enough product in your palm to cover hands and rub together thoroughly until dry. Children under the age of 5 should be supervised by an adult when using this product.

WARNINGS

For external use only. Flammable. Keep away from heat or flame.

Do not use -in children less than 2 years of age -on open skin wounds.

When using this product - keep out of eyes. If contact occurs, rinse thoroughly with water.

Stop use and ask a doctor if -irritation and redness develop.

INACTIVE INGREDIENT

Purified water, Witch Hazel Extract, Safflower oleosomes in glycerin and aqua, Hydroxypropyl Methylcellulose, Cedarwood Essential Oil, Lavender Essential Oil, Rosemary Essential Oil, Lemon Essential Oil, Orange Essential Oil, Aloe Vera Powder 200X (certified organic).

INDICATIONS AND USAGE

To help reduce bacteria on the skin.

PURPOSE

Antimicrobial